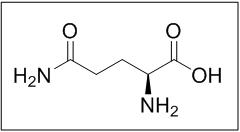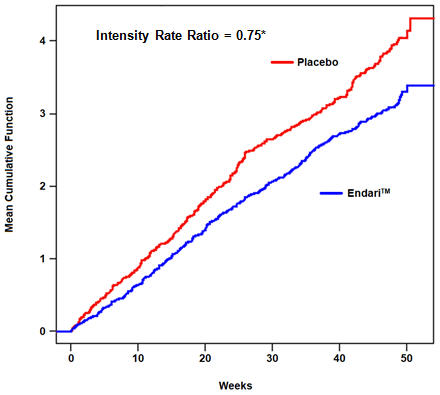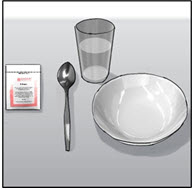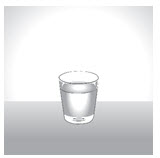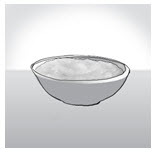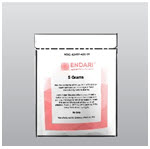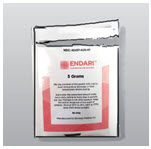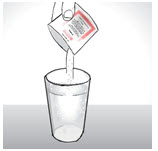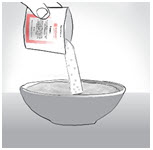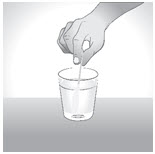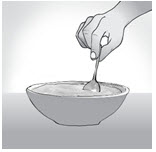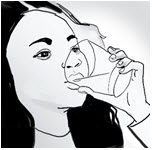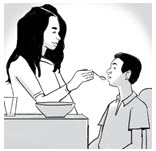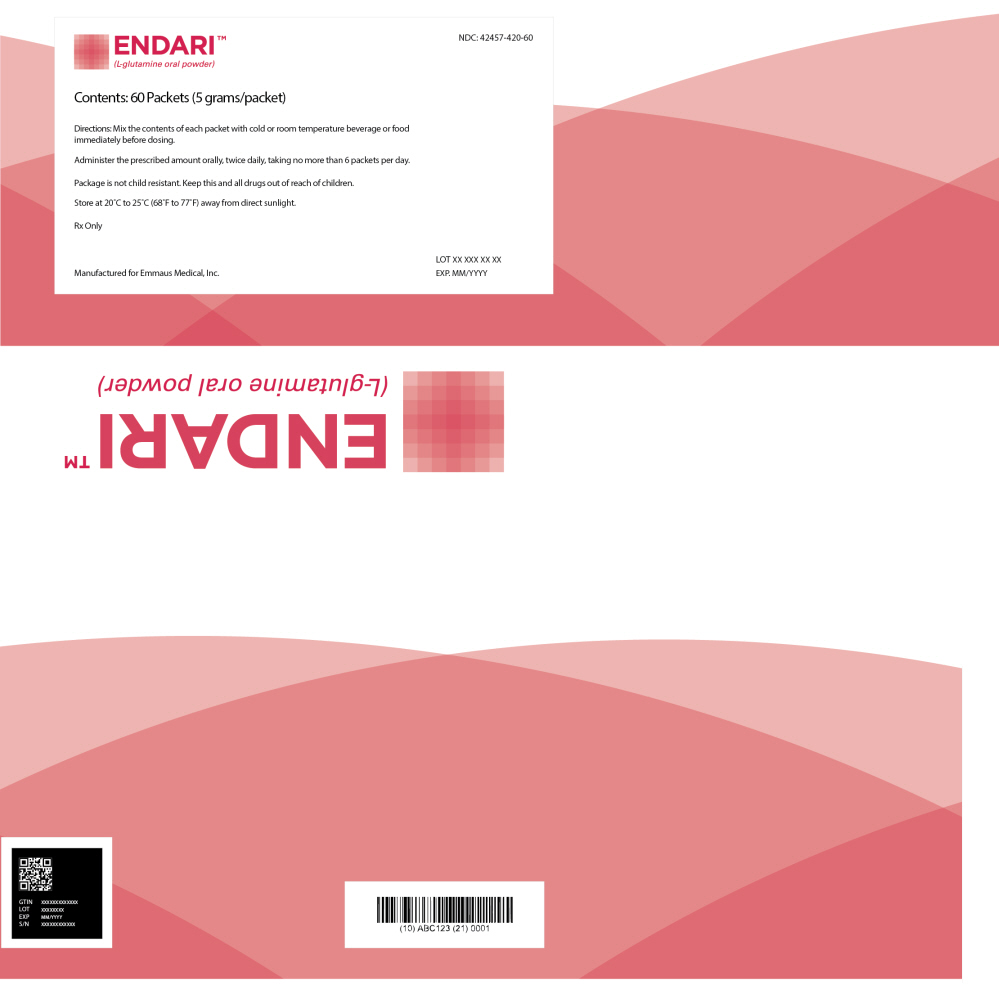 DRUG LABEL: Endari
NDC: 42457-420 | Form: POWDER, FOR SOLUTION
Manufacturer: Emmaus Medical, Inc.
Category: prescription | Type: HUMAN PRESCRIPTION DRUG LABEL
Date: 20250620

ACTIVE INGREDIENTS: Glutamine 5 g/1 1

HIGHLIGHTS OF PRESCRIBING INFORMATION

These highlights do not include all the information needed to use ENDARI™ safely and effectively. See full prescribing information for ENDARI.
ENDARI (L-glutamine oral powder)
Initial U.S. Approval: 2017

1 INDICATIONS AND USAGE

ENDARI is an amino acid indicated to reduce the acute complications of sickle cell disease in adult and pediatric patients 5 years of age and older. (1)

2 DOSAGE AND ADMINISTRATION

- 5 grams to 15 grams orally, twice daily based on body weight. (2)
- Each dose of Endari should be mixed in 8 oz. (240 mL) of cold or room temperature beverage or 4 oz. to 6 oz. of food before ingestion. (2)

3 DOSAGE FORMS AND STRENGTHS

Oral Powder: 5 grams of L-glutamine powder per paper-foil-plastic laminate packet. (3)

4 CONTRAINDICATIONS

None (4)

6 ADVERSE REACTIONS

Most common adverse reactions (incidence > 10%) are constipation, nausea, headache, abdominal pain, cough, pain in extremity, back pain, and chest pain. (6)

To report SUSPECTED ADVERSE REACTIONS, contact Emmaus Medical, Inc. at 1-877-420-6493 or FDA at 1-800-FDA-1088 or www.fda.gov/medwatch

FULL PRESCRIBING INFORMATION

1 INDICATIONS AND USAGE

Endari is indicated to reduce the acute complications of sickle cell disease in adult and pediatric patients 5 years of age and older.

2 DOSAGE AND ADMINISTRATION

2.1 Dosage

Administer Endari orally, twice per day at the dose based on body weight according to Table 1.

Table 1. Recommended Dosing
Weight in kilograms | Weight in pounds | Per dose in grams | Per day in grams | Packets per dose | Packets per day
less than 30 | less than 66 | 5 | 10 | 1 | 2
30 to 65 | 66 to 143 | 10 | 20 | 2 | 4
greater than 65 | greater than 143 | 15 | 30 | 3 | 6

2.2 Preparation of Product

Mix Endari immediately before ingestion with 8 oz. (240 mL) of cold or room temperature beverage, such as water, milk or apple juice, or 4 oz. to 6 oz. of food such as applesauce or yogurt. Complete dissolution is not required prior to administration.

3 DOSAGE FORMS AND STRENGTHS

Oral powder: 5 grams of L–glutamine as a white crystalline powder in paper-foil-plastic laminate packets

4 CONTRAINDICATIONS

None

6 ADVERSE REACTIONS

6.1 Clinical Trials Experience

Because clinical trials are conducted under widely varying conditions, adverse reaction rates observed in the clinical trials of a drug cannot be directly compared to rates in the clinical trials of another drug and may not reflect the rates observed in practice.

The data described below reflect exposure to Endari in 187 patients, including 136 exposed for 6 months and 109 exposed for ≥1 year. Endari was studied in 2 placebo-controlled clinical trials (a phase 3 study, n=230 and a phase 2 study, n=70). In these trials, patients with sickle cell anemia or sickle β^0-thalassemia were randomized to receive Endari (n=187) or placebo (n=111) orally twice daily for 48 weeks followed by 3 weeks of tapering. Both studies included pediatric and adult patients (5-58 years of age) and 54% were female. The majority of patients were black (97.3%), had a diagnosis of sickle cell anemia (89.9%) and were receiving hydroxyurea at baseline (63.4%).

Treatment discontinuation due to adverse reactions was reported in 2.7% (n=5) of patients receiving Endari. These adverse reactions included one case each of hypersplenism, abdominal pain, dyspepsia, burning sensation, and hot flash.

Serious adverse reactions were reported in both treatment groups, more frequently in the placebo group, and were consistent with the underlying disease.

Three deaths (3/187=1.6%) occurred during the study in the Endari treatment group as compared to none in the placebo treatment group. None of the deaths were considered to be related to Endari treatment. Adverse reactions occurring in greater than 10% of patients treated with Endari are shown in Table 2 below.

Table 2. Adverse Reactions Occurring at an Incidence > 10% in Clinical Studies of Endari
Adverse reaction | Endari N = 187 (%) | Placebo N = 111 (%)
Constipation | 21 | 18
Nausea | 19 | 14
Headache | 18 | 15
Abdominal Pain [Abdominal pain = abdominal pain and abdominal pain, upper] | 17 | 16
Cough | 16 | 14
Pain in extremity | 13 | 7
Back pain | 12 | 5
Chest pain | 12 | 8

8 USE IN SPECIFIC POPULATIONS

8.1 Pregnancy

Risk Summary

There are no available data on Endari use in pregnant women to inform a drug-associated risk of major birth defects and miscarriage. Animal reproduction studies were not conducted with Endari.

Adverse outcomes in pregnancy occur regardless of the health of the mother or the use of medications. The background risk of major birth defects and miscarriage for the indicated population are unknown. In the U.S. general population, the estimated background risk of major birth defects and miscarriage in clinically recognized pregnancies is 2% to 4% and 15% to 20%, respectively.

8.2 Lactation

Risk Summary

There are no data on the presence of Endari in human milk, the effect on the breastfed infant or the effect on milk production. The developmental and health benefits from breastfeeding should be considered along with the mother's clinical need for Endari and any potential adverse effects on the breastfed child from Endari or from the underlying maternal condition.

8.4 Pediatric Use

The safety and effectiveness of Endari have been established in pediatric patients 5 years and older. Use of Endari is supported by evidence from 2 placebo-controlled studies in adult and pediatric patients with sickle cell disease. The clinical studies enrolled 110 pediatric patients in the following age groups: 46 children (5 years up to less than 12 years) and 64 adolescents (12 years to less than 17 years).

The safety and effectiveness of Endari in pediatric patients with sickle cell disease younger than 5 years old has not been established.

8.5 Geriatric Use

Clinical studies of Endari did not include sufficient numbers of subjects aged 65 and over to determine whether they respond differently from younger subjects. Other reported clinical experience has not identified differences in responses between the elderly and younger patients. In general, dose selection for an elderly patient should be cautious, usually starting at the low end of the dosing range, reflecting the greater frequency of decreased hepatic, renal, or cardiac function, and of concomitant disease or other drug therapy.

10 OVERDOSAGE

Single oral doses of L-glutamine at about 20 g/kg to 22 g/kg, 8 g/kg to 11 g/kg, and 19 g/kg were lethal in mice, rats, and rabbits, respectively. Supportive measures should be undertaken in the event of overdose of Endari.

11 DESCRIPTION

Endari (L-glutamine) is an amino acid. L-glutamine is designated chemically as (S)-2-aminoglutaramic acid, L-glutamic acid 5-amide, or (S)-2,5-diamino-5-oxopentanoic acid. The molecular formula is C5H10N2O3 with the molecular weight of 146.15 g/mol and the following structural formula:

Endari is formulated as a white crystalline powder and is packaged as 5 grams in a paper-foil-plastic laminate packet for oral administration.

12 CLINICAL PHARMACOLOGY

12.1 Mechanism of Action

The mechanism of action of the amino acid L-glutamine in treating sickle cell disease (SCD) is not fully understood. Oxidative stress phenomena are involved in the pathophysiology of SCD. Sickle red blood cells (RBCs) are more susceptible to oxidative damage than normal RBCs, which may contribute to the chronic hemolysis and vaso-occlusive events associated with SCD. The pyridine nucleotides, NAD^+ and its reduced form NADH, play roles in regulating and preventing oxidative damage in RBCs. L-glutamine may improve the NAD redox potential in sickle RBCs through increasing the availability of reduced glutathione.

12.2 Pharmacodynamics

In vivo analyses demonstrated that L-glutamine supplementation improved NAD redox potential.

12.3 Pharmacokinetics

The pharmacokinetics of L-glutamine has been studied in healthy subjects and a variety of disease states. Relevant results from published literature are summarized below.

Absorption

Following single-dose oral administration of L-glutamine at 0.1 g/kg, mean peak L-glutamine concentration was 1028 µM (or 150 mcg/mL) occurring approximately 30 minutes after administration.

The pharmacokinetics following multiple oral doses at 0.1 g/kg, 0.3 g/kg, and 0.6 g/kg found peak concentrations increasing with each dose, but maximum concentration did not increase proportionally to the dose, suggesting a saturable absorption process. The peak concentration was seen occurring approximately one hour after administration. There was no accumulation of L-glutamine levels upon multiple oral doses administered twice-daily.

Effect of Food

No significant change in L-glutamine concentration was associated with food, suggesting that L-glutamine can be taken with or without food.

Distribution

After multiple oral doses, the apparent volume of distribution was estimated to be approximately 750 mL/kg.

Elimination

After an intravenous bolus dose, the terminal elimination half-life of L-glutamine was approximately one hour.

Metabolism

Endogenous L-glutamine participates in various metabolic activities, including the formation of glutamate, and synthesis of proteins, nucleotides, and amino sugars. Exogenous L-glutamine is anticipated to undergo similar metabolism.

Excretion

Metabolism is the major route of disappearance for L-glutamine from the plasma. Urinary excretion of L-glutamine was less than 0.3% of the administered dose in intravenous infusion studies.

Specific Populations

In a population pharmacokinetic analysis, body weight was found to be a significant covariate of L-glutamine exposures supporting the tiered body weight based dosing of Endari. The pharmacokinetics of Endari has not been studied in subjects with renal or hepatic impairment.

Drug Interactions

No drug interaction studies have been conducted.

13 NONCLINICAL TOXICOLOGY

13.1 Carcinogenesis, Mutagenesis, Impairment of Fertility

Long-term studies in animals have not been performed to evaluate the carcinogenic potential of L-glutamine.

L-glutamine was not mutagenic in a bacterial mutagenicity (Ames) assay, nor clastogenic in a chromosome aberration assay in mammalian (Chinese Hamster Lung CHL/IU) cells.

Animal reproduction studies and its potential for impairment of fertility have not been conducted with L-glutamine . It is also not known whether L-glutamine can cause fetal harm when administered to a pregnant woman or whether it can affect reproductive capacity.

14 Clinical Studies

The efficacy of Endari in sickle cell disease was evaluated in a randomized, double-blind, placebo-controlled, multi-center clinical trial entitled "A Phase III Safety and Efficacy Study of L-Glutamine to Treat Sickle Cell Disease or Sickle βo-thalassemia" [NCT01179217] (see Table 3).

The clinical trial evaluated the efficacy and safety of Endari in 230 patients (5 to 58 years of age) with sickle cell anemia or sickle β^0-thalassemia who had 2 or more painful crises within 12 months prior to enrollment. Eligible patients stabilized on hydroxyurea for at least 3 months continued their therapy throughout the study. The trial excluded patients who had received blood products within 3 weeks, had renal insufficiency or uncontrolled liver disease, or were pregnant (or planning pregnancy) or lactating. Study patients received Endari or placebo for a treatment duration of 48 weeks followed by 3 weeks of tapering. Efficacy was demonstrated by a reduction in the number of sickle cell crises through Week 48 and prior to the start of tapering among patients that received Endari compared to patients who received placebo. This clinical benefit was observed irrespective of hydroxyurea use. A sickle cell crisis was defined as a visit to an emergency room/medical facility for sickle cell disease-related pain which was treated with a parenterally administered narcotic or parenterally administered ketorolac. In addition, the occurrence of chest syndrome, priapism, and splenic sequestration were considered sickle cell crises. Treatment with Endari also resulted in fewer hospitalizations due to sickle cell pain at Week 48, fewer cumulative days in hospital and a lower incidence of acute chest syndrome.

Table 3. Results from the Endari Clinical Trial in Sickle Cell Disease
Event | Endari (n = 152) | Placebo (n = 78)
Median number of sickle cell crises (min,max) [Measured through 48 weeks of treatment] | 3 (0, 15) | 4 (0, 15)
Median number of hospitalizations for sickle cell pain (min, max) | 2 (0, 14) | 3 (0, 13)
Median cumulative days hospitalized (min, max) | 6.5 (0, 94) | 11 (0, 187)
Median time (days) to first sickle cell crisis (95% CI), [Hazard Ratio=0.69 (95% CI=0.52, 0.93), estimated based on unstratified Cox's proportional model. Median time and 95% CI were estimated based on the Kaplan Meier method.] | 84 (62, 109) | 54 (31, 73)
Patients with occurrences of acute chest syndrome (%) | 13 (8.6%) | 18 (23.1%)

The recurrent crisis event time analysis (Figure 1) yielded an intensity rate ratio (IRR) value of 0.75 with 95% CI= (0.62, 0.90) and (0.55, 1.01) based on unstratified models using the Andersen-Gill and Lin, Wei, Yang and Ying methods, respectively in favor of Endari, suggesting that over the entire 48-week period, the average cumulative crisis count was reduced by 25% from the Endari group over the placebo group.

Figure 1. Recurrent Event Time for Sickle Cell Crises by Treatment Group

*Andersen-Gill: 95% CI (0.62, 0.90); Lin-Wei-Yang-Ying: 95% CI (0.55, 1.01)

16 HOW SUPPLIED/STORAGE AND HANDLING

Endari is supplied in paper-foil-plastic laminate packets containing 5 grams of L-glutamine white crystalline powder.

- Carton of 60 packets: NDC 42457-420-60

STORAGE AND HANDLING

Store at 20°C to 25°C (68°F to 77°F) away from direct sunlight.

17 PATIENT COUNSELING INFORMATION

Advise the patient to read the FDA-approved patient labeling (Instructions for Use).

Dosage and Administration

Advise patient to take a missed dose as soon as they remember. Patient should not double the dose that they take.

Instruct patient to mix each dose in 8 oz. (240 mL) of cold or room temperature beverage or 4 to 6 oz. of food.

Advise patient that complete dissolution is not required prior to administration.

Manufactured for:
Emmaus Medical, Inc
Torrance, CA 90503

INSTRUCTIONS FOR USE

ENDARI® (en-dar-ee)
(L-glutamine oral powder)

Read this Instructions for Use before you start taking Endari and each time you get a refill. There may be new information. This Instructions for Use does not take the place of talking to your healthcare provider about your medical condition or treatment. You and your healthcare provider should talk about Endari before you start taking it and at regular checkups.

Endari is usually taken 2 times a day. Take Endari as prescribed by your healthcare provider.

You will need the following supplies to mix and take Endari:

- Your prescribed dose of Endari (1, 2, or 3 packets as directed by your healthcare provider) .
- a clean cup or small bowl
- a spoon

You can mix Endari:

- with a liquid, such as water, milk, or apple juice Or
- with food, such as applesauce or yogurt

How to mix and take a dose of Endari.

Mixing with Liquid

Mixing with Food

Step 1:
Fill a cup with 8 ounces (240 mL) of liquid or a small bowl with 4 to 6 ounces of food.
The food or liquid should be cold or room temperature.
Do not use a hot food or liquid.

Step 2:
Find the perforations at the top of each side of the Endari packet.
Use the perforations to fully tear open each Endari packet.

Step 3:
Pour the contents of the Endari packet into the cup or bowl.
If more than 1 packet is needed, repeat steps 2 and 3 above for all of the packets needed to prepare your prescribed does of Endari.

Step 4:
Use the spoon to mix the prescribed dose of Endari with the liquid or food.
Endari may not fully dissolve. You can take your dose of Endari even if it does not fully dissolve.

Step 5:
Drink or eat the prescribed dose of Endari right away after mixing it.
Do not store the Endari mixture for later use.

If you miss a dose of Endari, take the missed dose as soon as you remember. Do not double the dose to make up for a missed dose.

How should I store Endari?

- Store Endari at room temperature between 68°F to 77°F (20°C to 25°C).
- Keep Endari away from direct sunlight.

Keep Endari and all medicines out of the reach of children.

Manufactured for:
Emmaus Medical, Inc.
Torrance, CA 90503

For more information got to www.EnadriRx.com or call 1-877-420-6493.

This Instructions for Use has been approved by the U.S. Food and Drug Administration.

Issued: 04/2020

PRINCIPAL DISPLAY PANEL - 5 gram Packet Carton

NDC: 42457-420-60

ENDARI™
(L-glutamine oral powder)

Contents: 60 Packets (5 grams/packet)

Directions: Mix the contents of each packet with cold or room temperature beverage or food
immediately before dosing.

Administer the prescribed amount orally, twice daily, taking no more than 6 packets per day.

Package is not child resistant. Keep this and all drugs out of reach of children.

Store at 20°C to 25°C (68°F to 77°F) away from direct sunlight.

Rx Only

LOT XX XXX XX XX
EXP. MM/YYYY

Manufactured for Emmaus Medical, Inc.